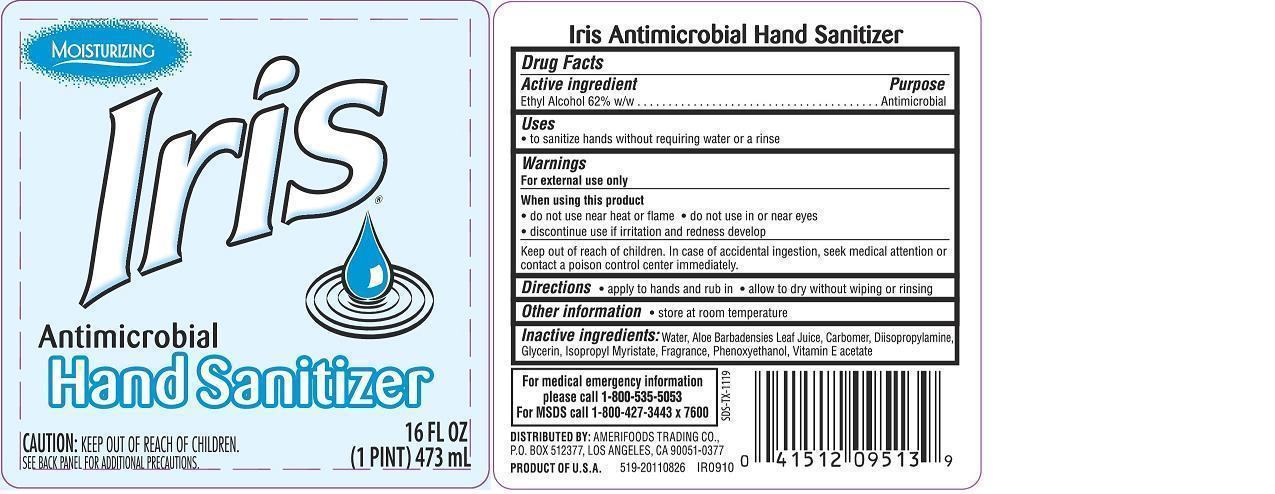 DRUG LABEL: IRIS ANTIMICROBIAL HAND SANITIZER
NDC: 59860-519 | Form: SOAP
Manufacturer: Smart and Final Stores
Category: otc | Type: HUMAN OTC DRUG LABEL
Date: 20131015

ACTIVE INGREDIENTS: ALCOHOL 0.62 mL/1 mL
INACTIVE INGREDIENTS: WATER; CARBOMER HOMOPOLYMER TYPE C (ALLYL PENTAERYTHRITOL CROSSLINKED); GLYCERIN; ALOE VERA LEAF; ISOPROPYL MYRISTATE; PHENOXYETHANOL; .ALPHA.-TOCOPHEROL ACETATE; DIISOPROPYLAMINE

Active ingredient

Ethyl Alcohol 62 % w/w

Purpose

Antimicrobial

Keep out of reach of children

In case of accidental ingestion, seek medical attention or contact a poison control center immediately.

Uses

 to sanitize hands without requiring water or a rinse

Warnings For external use only

When using this product

 do not use near heat or flame

 do not use in or near eyes

 discontinue use if irritation and redness develop

Directions

 apply to hands and rub in  allow to dry without wiping or rinsing

Other information

 store at room temperature

Inactive ingredients:

Water, Aloe Barbadensies Leaf Juice, Carbomer, Diisopropylamine, Glycerin, Isopropyl Myristate, Fragrance, Phenoxyethanol, Tocopheryl Acetate.